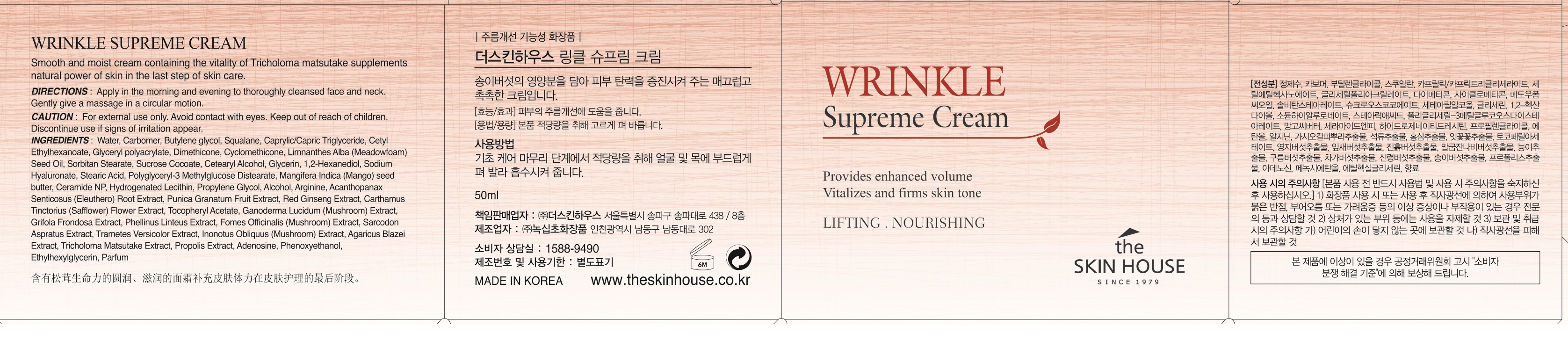 DRUG LABEL: THE SKINHOUSE WRINKLE SUPREMECREAM
NDC: 73590-0005 | Form: CREAM
Manufacturer: NOKSIBCHO cosmetic Co., Ltd.
Category: otc | Type: HUMAN OTC DRUG LABEL
Date: 20200129

ACTIVE INGREDIENTS: ASIAN GINSENG 0.5 g/100 mL
INACTIVE INGREDIENTS: WATER; BUTYLENE GLYCOL

Drug Facts

ACTIVE INGREDIENT

Panax Ginseng Root Extract, Ganoderma Lucidum (Mushroom) Extract, Phellinus Linteus Extract, Inonotus Obliquus (Mushroom) Extract, Agaricus Blazei Extract, Tricholoma Matsutake Extract, Hizikia Fusiforme Extract, Codium Tomentosum Extract, Gelidium Cartilagineum Extract.

INACTIVE INGREDIENT

Water
Carbomer
Carbomer
Butylene glycol
Cetyl Ethylhexanoate
Caprylic/Capric Triglyceride
Glycerin
Sodium Hyaluronate
Glyceryl Stearate
PEG-100 Stearate
Glyceryl polyacrylate
Dimethicone
Cyclomethicone
1,2-Hexanediol
Cetearyl Alcohol
Sorbitan Stearate
Squalane
Polysorbate 80
Butyrospermum Parkii (Shea Butter)
Tocopheryl Acetate
Dimethicone
Acanthopanax Senticosus (Eleuthero) Root Extract
Punica Granatum Fruit Extract
Panax Ginseng Root Extract
Carthamus Tinctorius (Safflower) Flower Extract
Panax Ginseng Root Extract
Arginine
Ganoderma Lucidum (Mushroom) Extract
Grifola Frondosa Extract
Phellinus Linteus Extract
Fomes Officinalis (Mushroom) Extract
Sarcodon Aspratus Extract
Trametes Versicolor Extract
Inonotus Obliquus (Mushroom) Extract
Agaricus Blazei Extract
Tricholoma Matsutake Extract
Propolis Extract
Xanthan GUM
Adenosine
Ethylhexylglycerin
Parfum

PURPOSE

All skin types, especially for those who wants to improve and prevent wrinkles

The ginseng extract and 9 types of mushroom extracts will fill up skin with nutrition. You will feel the elasticity once you apply cream onto your skin.

It contains the mushroom extract which has antioxidant ingredients for anti-aging and anti-wrinkle. And it also contains ginseng ingredients which is full of nutrition. It will help skin to relieve stress from external environment and help skin to look vital, radiant and elastic.

Must have cream for recovery of skin fatigue and skin care

keep out of reach of the children

INDICATIONS AND USAGE

After cleansing, use toner to smooth the skin texture.

Apply the serum or the emulsion to the face, and let it be absorbed deeply into skin.

Apply a small amount of the cream to the face, and spread it along the skin texture

WARNINGS

For external use only
When using this product

■ if the following symptoms occurs after use, stop use and consult with a skin specialist

red specks, swelling, itching

■ don’t use on the part where there is injury, eczema, or dermatitis

Keep out of reach of children

■ if swallowed, get medical help or contact a person control center immediately

DOSAGE AND ADMINISTRATION

for external use only